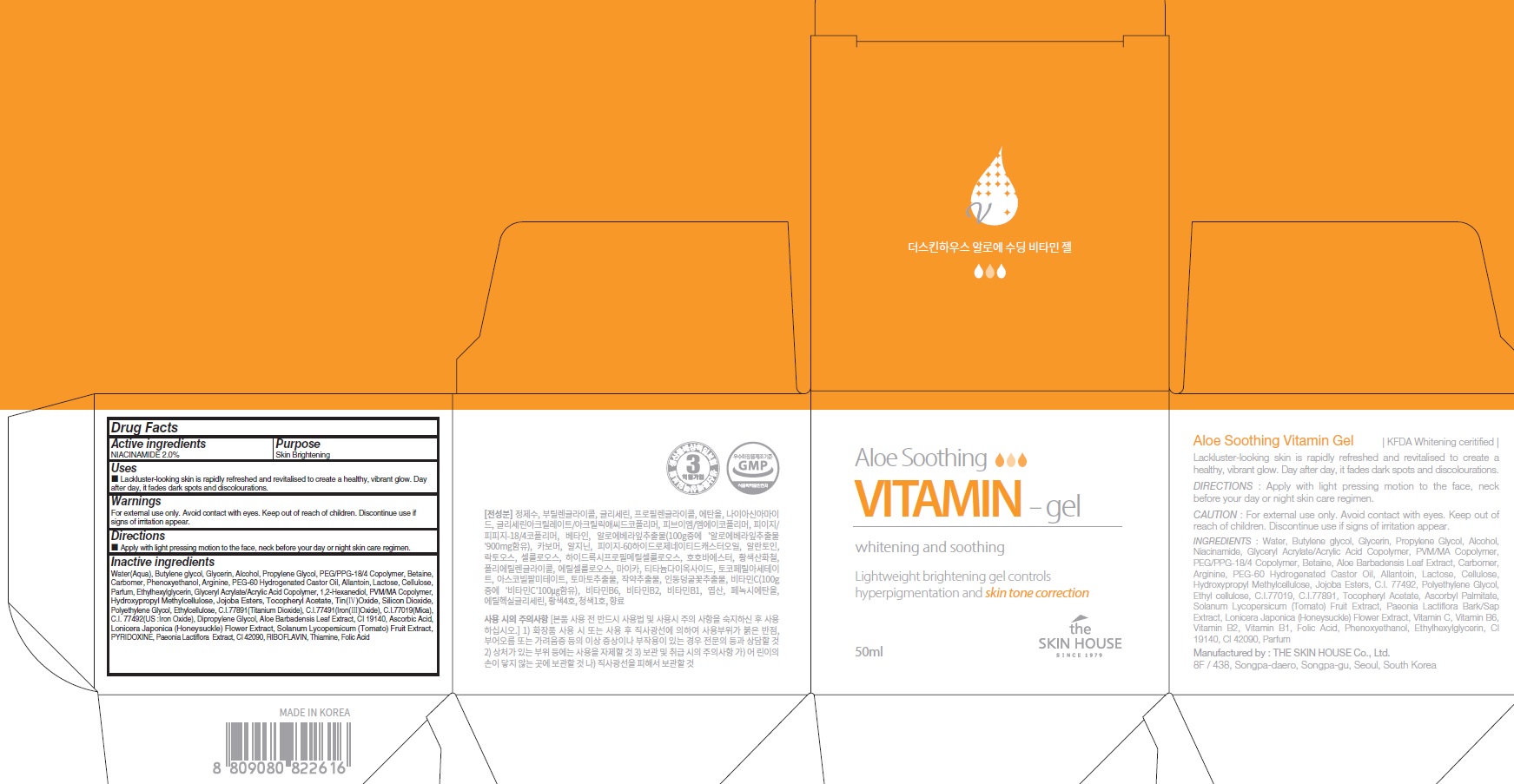 DRUG LABEL: THE SKINHOUSE ALOE SOOTHING VITAMIN
NDC: 73590-0075 | Form: GEL
Manufacturer: NOKSIBCHO cosmetic Co., Ltd.
Category: otc | Type: HUMAN OTC DRUG LABEL
Date: 20210714

ACTIVE INGREDIENTS: NIACINAMIDE 1.0 g/50 mL
INACTIVE INGREDIENTS: Water; Butylene Glycol; Glycerin

Drug Facts

ACTIVE INGREDIENT

NIACINAMIDE 2.0%

INACTIVE INGREDIENTS

Water(Aqua), Butylene glycol, Glycerin, Alcohol, Propylene Glycol, PEG/PPG-18/4 Copolymer, Betaine, Carbomer, Phenoxyethanol, Arginine, PEG-60 Hydrogenated Castor Oil, Allantoin, Lactose, Cellulose, Parfum, Ethylhexylglycerin, Glyceryl Acrylate/Acrylic Acid Copolymer, 1,2-Hexanediol, PVM/MA Copolymer, Hydroxypropyl Methylcellulose, Jojoba Esters, Tocopheryl Acetate, Tin(Ⅳ)Oxide, Silicon Dioxide, Polyethylene Glycol, Ethylcellulose, C.I.77891(Titanium Dioxide), C.I.77491(Iron(Ⅲ)Oxide), C.I.77019(Mica), C.I. 77492(US :Iron Oxide), Dipropylene Glycol, Aloe Barbadensis Leaf Extract, CI 19140, Ascorbic Acid, Lonicera Japonica (Honeysuckle) Flower Extract, Solanum Lycopersicum (Tomato) Fruit Extract, PYRIDOXINE, Paeonia Lactiflora Extract, CI 42090, RIBOFLAVIN, Thiamine, Folic Acid

PURPOSE

Skin Brightening

WARNINGS

For external use only.
Avoid contact with eyes.
Keep out of reach of children.
Discontinue use if signs of irritation appear.

KEEP OUT OF REACH OF CHILDREN

Uses

■ Lackluster-looking skin is rapidly refreshed and revitalised to create a healthy, vibrant glow. Day after day, it fades dark spots and discolourations.

Directions

■ Apply with light pressing motion to the face, neck before your day or night skin care regimen.